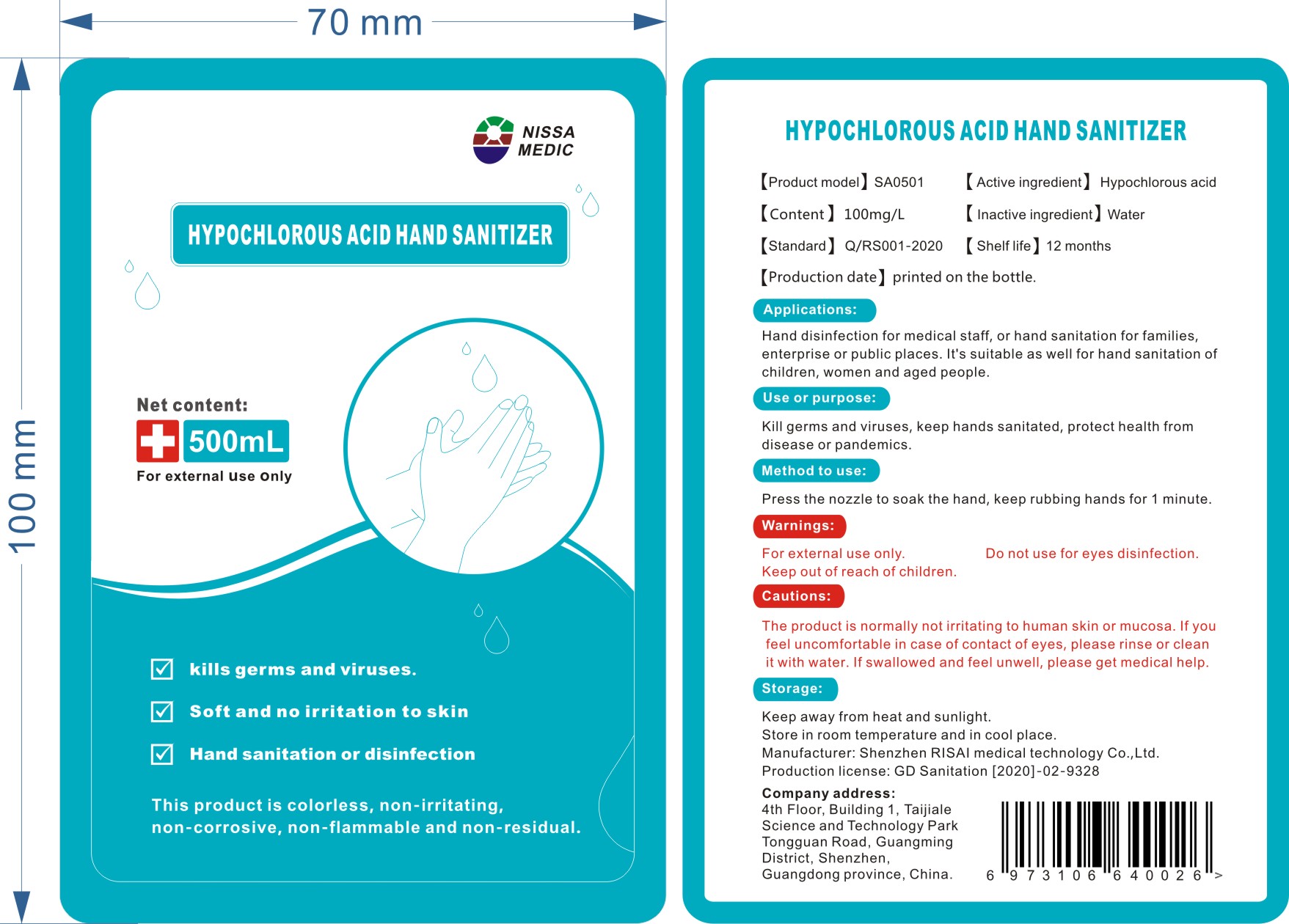 DRUG LABEL: Hypochlorous Acid Hand Sanitizer
NDC: 81934-101 | Form: LIQUID
Manufacturer: Shenzhen Risai Medical Technology Co., Ltd
Category: otc | Type: HUMAN OTC DRUG LABEL
Date: 20210525

ACTIVE INGREDIENTS: HYPOCHLOROUS ACID 50 mg/500 mL
INACTIVE INGREDIENTS: WATER

RiSai, Hypochlorous Acid Hand Sanitizer, Liquid, 500mL

Active ingredient

Hypochlorous acid 100 mg/L. Purpose: Sanitation.

Purpose

Kill germs and viruses, keep hands sanitated, protect health from disease or pandmics.

Use

Hand disinfection for medical staff, or hand sanitation of families, enterprise or public places. It's suitable as well for hand sanitation of children, women and aged people.

Warnings

For external use only.

Do not use for eyes disinfection.

Keep out of reach of children.

Do not use for eyes disinfection.

Cautions

The product is normally not irritation to human skin or mucosa. If you feel uncomfortable in case of contact of eyes, please rinse or clean it with water. If swallowed and fee unwell, please get medical help.

Stop use

If you feel uncomfortable in case of contact of eyes, please rinse or clean it with water. If swallowed and fee unwell, please get medical help.

Keep out of reach of children

Method to use

Press the nozzle to soak the hand, keep rubbing hands for 1 minute.

Storage

Keep away from heat and sunlight.

Store in room temperature and in cool place.

Inactive ingredient

Water